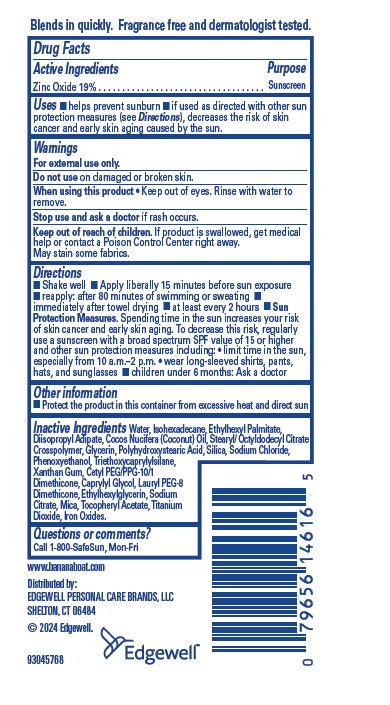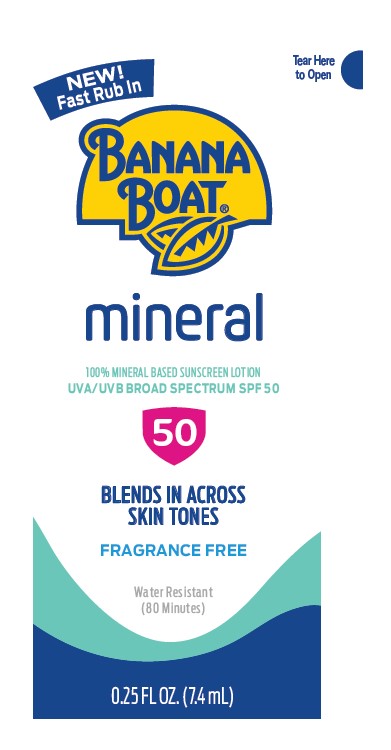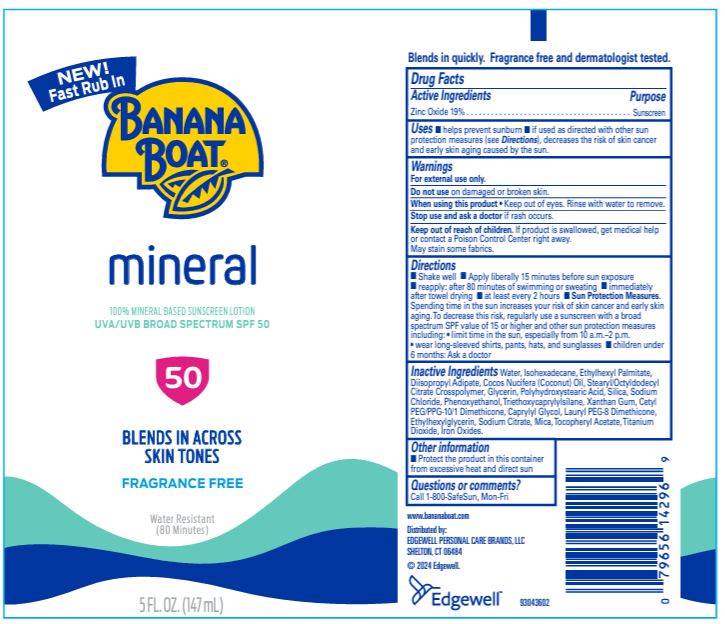 DRUG LABEL: Banana Boat
NDC: 63354-373 | Form: LOTION
Manufacturer: Edgewell Personal Care Brands LLC
Category: otc | Type: HUMAN OTC DRUG LABEL
Date: 20241030

ACTIVE INGREDIENTS: ZINC OXIDE 19 g/100 g
INACTIVE INGREDIENTS: MICA; CAPRYLYL GLYCOL; WATER; ETHYLHEXYLGLYCERIN; SODIUM CITRATE; .ALPHA.-TOCOPHEROL ACETATE; FERRIC OXIDE YELLOW; ETHYLHEXYL PALMITATE; TRIETHOXYCAPRYLYLSILANE; LAURYL PEG-8 DIMETHICONE (300 CPS); PHENOXYETHANOL; SODIUM CHLORIDE; XANTHAN GUM; TITANIUM DIOXIDE; GLYCERIN; DIISOPROPYL ADIPATE; POLYHYDROXYSTEARIC ACID (2300 MW); SILICON DIOXIDE; CETYL PEG/PPG-10/1 DIMETHICONE (HLB 2); ISOHEXADECANE; COCONUT OIL; STEARYL/OCTYLDODECYL CITRATE CROSSPOLYMER

Active Ingredients

Zinc Oxide 19.0%

Purpose

Sunscreen

Uses

Helps prevent sunburn. If used as directed with other sun Sunscreen protection measures (see Directions), decreases the risk of skin cancer and early skin aging caused by the sun.

Warnings

For external use only.

May stain some fabric.

Do Not Use

on damaged or broken skin.

When using this product

• Keep out of eyes. Rinse with water to remove.

Stop use and ask a doctor

if rash occurs.

Keep out of reach of children.

If product is swallowed, get medical help or contact a Poison Control Center right away. .

Directions

• Shake Well • Apply generously and evenly 15 minutes before sun exposure • Reapply at least every 2 hours • Sun Protection Measures: Spending time in the sun increases your risk of skin cancer and early skin aging. To decrease this risk, regularly use a sunscreen with a Broad Spectrum SPF value of 15 or higher and other sun protection measures including: ▪ limit time in the sun, especially from 10 a.m. - 2 p.m.; and ▪ wear long-sleeved shirts, pants, hats, and sunglasses. • Reapply after 80 minutes of swimming or sweating • Reapply immediately after towel drying.

Inactive Ingredients

Water, Isohexadecane, Ethylhexyl Palmitate, Diisopropyl Adipate, Cocos Nucifera (Coconut) Oil, Stearyl/Octyldodecyl Citrate Crosspolymer, Glycerin, Polyhydroxystearic Acid, Silica, Sodium Chloride, Phenoxyethanol, Triethoxycaprylylsilane, Xanthan Gum, Cetyl PEG/PPG‐10/1 Dimethicone, Caprylyl Glycol, Lauryl PEG‐8 Dimethicone, Ethylhexylglycerin, Sodium Citrate, Mica, Tocopheryl Acetate, Titanium Dioxide, Iron Oxides.

Other Information

Protect the product in this container from excessive heat and direct sun

Questions or Comments?

Call 1-800-SafeSun, Mon-Fri

Principal Display Panel

NEW!
Fast Rub In
Banana Boat
mineral
100% MINERAL BASED SUNSCREEN LOTION
UVA/UVB BROAD SPECTRUM SPF 50
50
BLENDS IN ACROSS SKIN TONES
FRAGRANCE FREE
Water Resistant
(80 minutes)
5 FL.OZ. (147 mL)

NEW!
Fast Rub In
Banana Boat
mineral
100% MINERAL BASED SUNSCREEN LOTION
UVA/UVB BROAD SPECTRUM SPF 50
50
BLENDS IN ACROSS SKIN TONES
FRAGRANCE FREE
Water Resistant
(80 minutes)
0.25 FL.OZ. (7.4 mL)